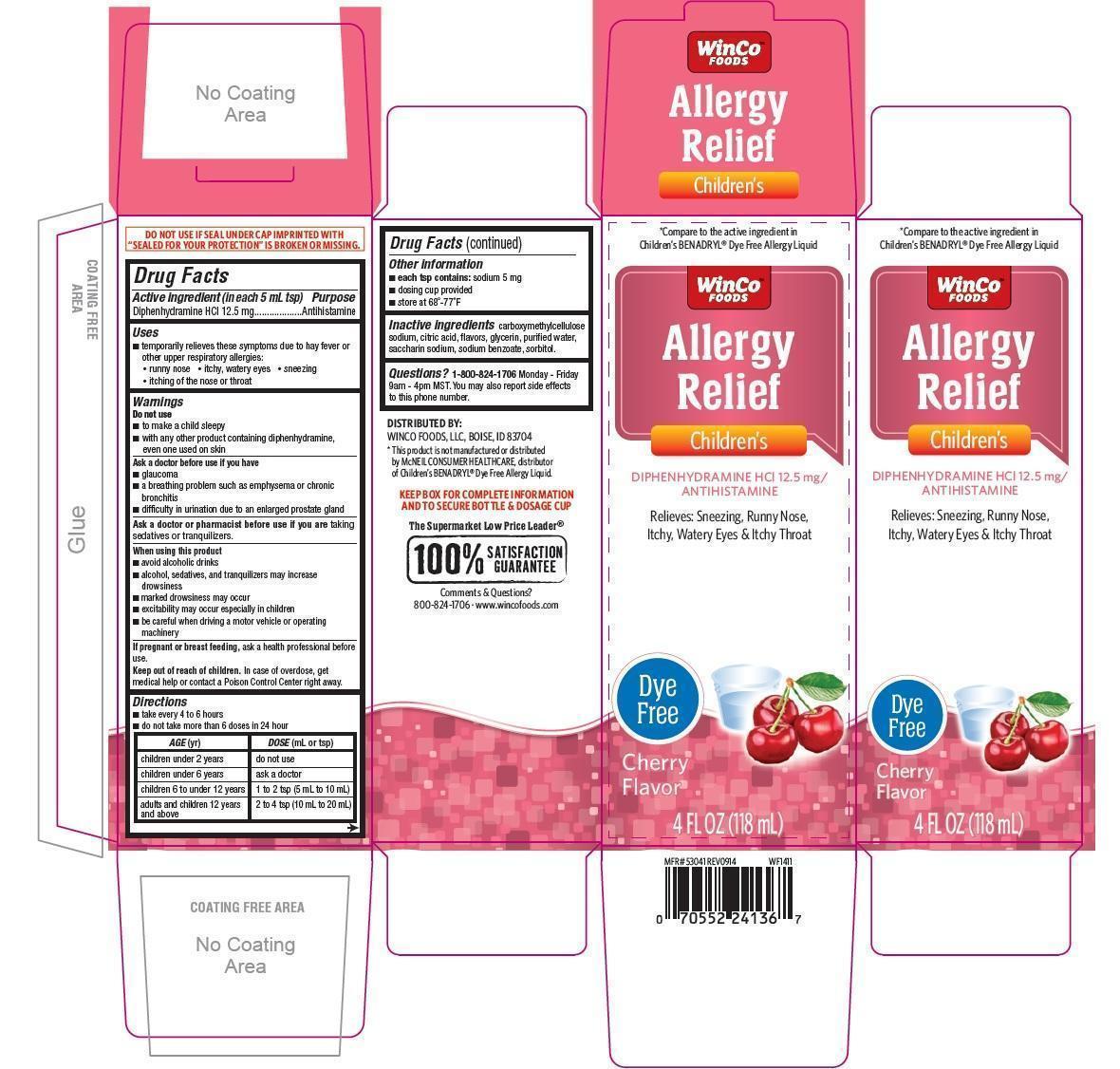 DRUG LABEL: Childrens Allergy Relief Dye Free Cherry
NDC: 67091-219 | Form: LIQUID
Manufacturer: WinCo Foods, LLC
Category: otc | Type: HUMAN OTC DRUG LABEL
Date: 20191209

ACTIVE INGREDIENTS: DIPHENHYDRAMINE HYDROCHLORIDE 12.5 mg/5 mL
INACTIVE INGREDIENTS: CARBOXYMETHYLCELLULOSE SODIUM; ANHYDROUS CITRIC ACID; GLYCERIN; WATER; SACCHARIN SODIUM; SODIUM BENZOATE; SORBITOL

Childrens Allergy Relief Dye Free Cherry Flavor

Active ingredient (in each 5 mL tsp)

Diphenhydramine HCl 12.5 mg

Purpose

Antihistamine

Uses

- temporarily relieves these symptoms due to hay fever or other upper respiratory allergies:
- runny nose
- itchy, watery eyes
- sneezing
- itching of the nose or throat

Warnings

Do not use

- to make a child sleepy
- with any other product containing diphenhydramine, even one used on skin

Ask a doctor before use if you have

- glaucoma
- a breathing problem such as emphysema or chronic bronchitis
- difficulty in urination due to an enlarged prostate gland

Ask a doctor or pharmacist before use if you are

taking sedatives or tranquilizers

When using this product

- avoid alcoholic drinks
- alcohol, sedatives, and tranquilizers may increase drowsiness
- marked drowsiness may occur
- excitability may occur especially in children
- be careful when driving a motor vehicle or operating machinery

If pregnant or breast feeding,

ask a health professional before use.

Keep out of reach of children. In case of overdose, get medical help or contact a Poison Control Center right away.

Directions

- take every 4 to 6 hours
- do not take more than 6 doses in 24 hours

Age (yr) | Dose (mL or tsp)
children under 2 years | do not use
children under 6 years | ask a doctor
children 6 to under 12 years | 1 to 2 tsp (5 mL to 10 mL)
adults and children 12 years and above | 2 to 4 tsp (10 mL to 20 mL)

Other information

- each tsp contains: sodium 5 mg
- dosing cup provided
- store at 68o - 77oF

Inactive ingredients

carboxymethylcellulose sodium, citric acid, flavors, glycerin, purified water, saccharin sodium, sodium benzoate, sorbitol

Questions?

1-800-824-1706 Monday -Friday 9am - 4pm MST.

You may also report side effects to this phone number

PDP

*Compare to the active ingredient in Children's BENADRYL Dye Free Allergy Liquid

WinCo Foods

Children's Allery Relief

Diphenhydramine HCl 12.5 mg/Antihistamine

Relieves: Sneezing, Runny Nose, Itchy, Watery Eyes & Itchy Throat

Dye Free

Cherry Flavor

4 fl oz (118 mL)